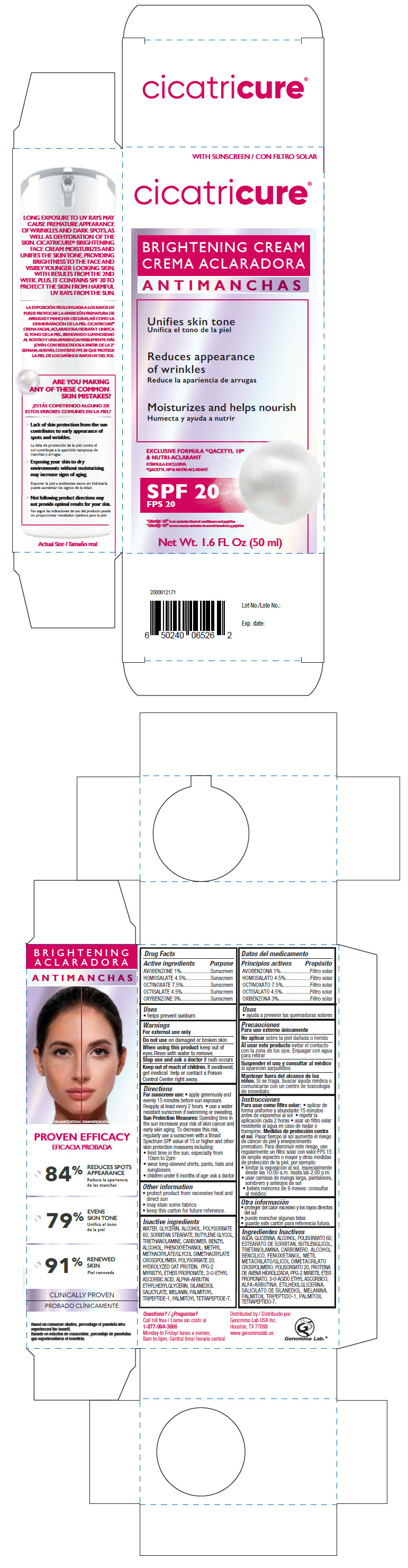 DRUG LABEL: Cicatricure Brightening With SPF
NDC: 50066-704 | Form: CREAM
Manufacturer: Genomma Lab USA Inc.
Category: otc | Type: HUMAN OTC DRUG LABEL
Date: 20241127

ACTIVE INGREDIENTS: Avobenzone 10 mg/1 mL; Homosalate 45 mg/1 mL; Octinoxate 75 mg/1 mL; Octisalate 45 mg/1 mL; Oxybenzone 30 mg/1 mL
INACTIVE INGREDIENTS: glycerin; Polysorbate 60; Polysorbate 20; Sorbitan Monostearate; Butylene glycol; CARBOMER HOMOPOLYMER, UNSPECIFIED TYPE

Cicatricure® Brightening Face Cream With SPF

Drug Facts

ACTIVE INGREDIENT

Active ingredients | Purpose
OCTINOXATE, 7.5% | Sunscreen
OCTISALATE, 4.5% | Sunscreen
HOMOSALATE, 4.5% | Sunscreen
OXYBENZONE, 3% | Sunscreen
AVOBENZONE, 1% | Sunscreen

Uses

- helps prevent sunburn
- if used as directed with other sun protection measures (see Directions), decreases the risk of skin cancer and early skin aging caused by the sun

Warnings

For external use only

Do not use on damaged or broken skin

When using this product keep out of eyes.

Rinse with water to remove.

Stop use and ask a doctor if rash occurs

Keep out of reach of children. If swallowed, get medical help or contact a Poison Control Center right away.

Directions

For sunscreen use

- apply generously and evenly 15 minutes before sun exposure. Reapply at least every 2 hours
- use a water resistant sunscreen if swimming or sweating.

Sun Protection Measures

Spending time in the sun increases your risk of skin cancer and early skin aging. To decrease this risk, regularly use a sunscreen with a Broad Spectrum SPF factor of 15 or higher and other skin protection measures including:

- limit time in the sun, especially from 10am to 2pm
- wear long-sleeved shirts, pants, hats and sunglasses
- children under 6 months of age: ask a doctor

Other information

- protect product from excessive heat and direct sun
- may stain some fabrics
- keep this carton for future reference.

Inactive ingredients

WATER, GLYCERIN, ALCOHOL, POLYSORBATE 60, SORBITAN STEARATE, BUTYLENE GLYCOL, TRIETHANOLAMINE, CARBOMER, BENZYL ALCOHOL, PHENOXYETHANOL, METHYL METHACRYLATE/GLYCOL DIMETHACRYLATE CROSSPOLYMER, FRAGRANCE, POLYSORBATE 20, HYDROLYZED OAT PROTEIN, PPG-2 MYRISTYL ETHER PROPIONATE, ETHYL ASCORBIC ACID, ALPHA-ARBUTIN, ETHYLHEXYLGLYCERIN, SILANEDIOL SALICYLATE, MELANIN, PALMITOYL TRIPEPTIDE-1, PALMITOYL TETRAPEPTIDE-7.

Questions

Call toll free 1 877-994-3666 Monday to Friday, 8am to 6pm, Central time

Distributed by:
Genomma Lab USA Inc.
Houston, TX 77098

PRINCIPAL DISPLAY PANEL - 50 ml Bottle Carton

WITH SUNSCREEN

cicatricure®
BRIGHTENING CREAM

Unifies skin tone

Reduces appearance
of wrinkles

Moisturizes and helps nourish

EXCLUSIVE FORMULA *QACETYL 10®
& NUTRI-ACLARANT

SPF 20

*QAcetyl-10® is an exclusive blend of conditioners and peptides

Net. Wt. 1.6 FL Oz (50 ml)